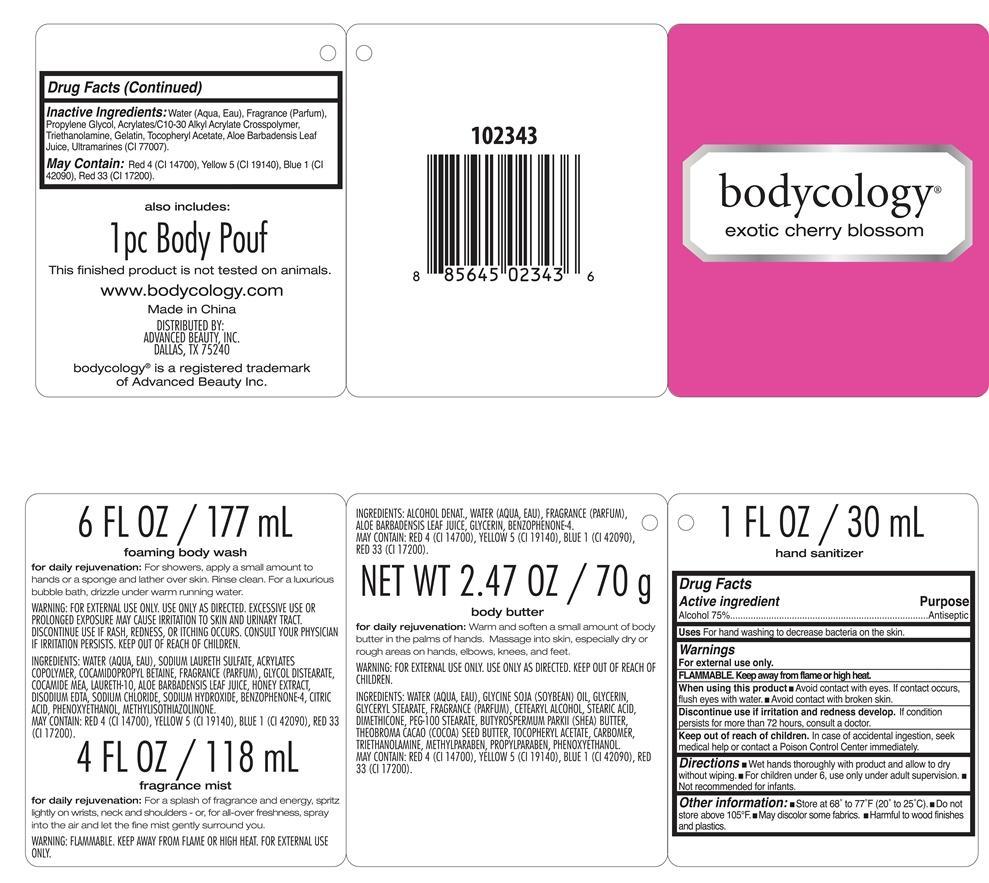 DRUG LABEL: exotic cherry blossom kit
NDC: 51345-107 | Form: KIT | Route: TOPICAL
Manufacturer: Advanced Beauty Systems, Inc.
Category: otc | Type: HUMAN OTC DRUG LABEL
Date: 20130702

ACTIVE INGREDIENTS: ALCOHOL 75 g/100 mL
INACTIVE INGREDIENTS: WATER; PROPYLENE GLYCOL; CARBOMER COPOLYMER TYPE A (ALLYL PENTAERYTHRITOL CROSSLINKED); TROLAMINE; GELATIN; .ALPHA.-TOCOPHEROL ACETATE; ALOE VERA LEAF; ULTRAMARINE BLUE

exotic cherry blossom 4 pc kit

Active Ingredient Purpose

Alcohol 75% Antiseptic

PURPOSE

Uses For hand washing to decrease bacteria on the skin

Keep out of reach of children. In case of accidental ingestion, seek medical help or contact a Poison Control Center immediately.

INDICATIONS AND USAGE

Discontinue use if irritation and redness develop. If condition persists for more than 72 hours, consult a doctor.

Warnings

For external use only

Flammable. Keep away from flame or high heat.

When using this product

- Avoid contact with eyes. If contact occurs flush eyes with water.
- Avoid contact with Broken skin

Directions

- Wet hands thoroughly with product and allow to dry without wiping
- For children under 6, use only under adult supervision
- Not recommeded for infants

INACTIVE INGREDIENT

Water (Aqua, Eau), Fragrance (Parfum), Propylene Glycol, Acrylates/C10-30 Alkyl Acrylate Crosspolymer, Triethanolamine, Gelatin, Tocopheryl Acetate, Aloe Barbadensis Leaf juice, Ultra marines (CI 77007)